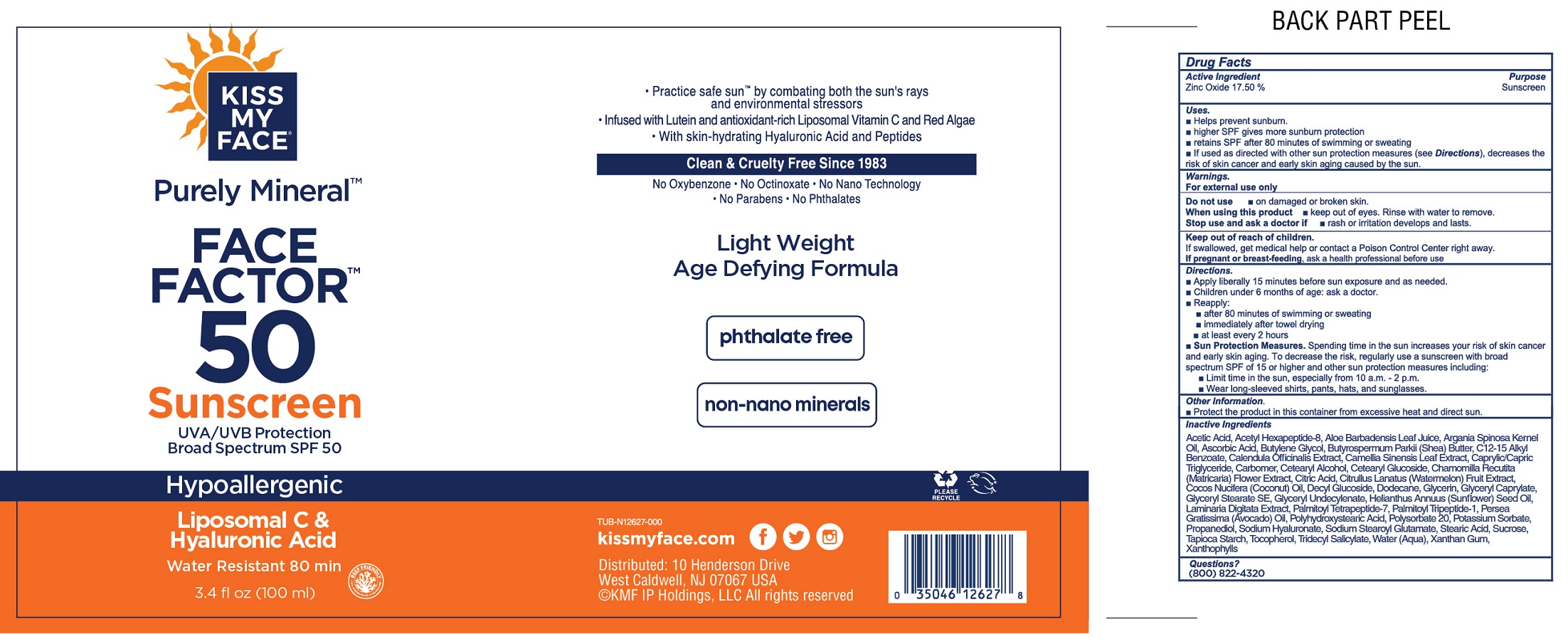 DRUG LABEL: Kiss My Face Purely Mineral Face Factor 50 Sunscreen SPF 50
NDC: 74154-902 | Form: LOTION
Manufacturer: Windmill Health Products, LLC
Category: otc | Type: HUMAN OTC DRUG LABEL
Date: 20260225

ACTIVE INGREDIENTS: ZINC OXIDE 175 mg/1 mL
INACTIVE INGREDIENTS: ACETIC ACID; ACETYL HEXAPEPTIDE-8 AMIDE; ALOE VERA LEAF JUICE; ARGAN OIL; ASCORBIC ACID; BUTYLENE GLYCOL; SHEA BUTTER; ALKYL (C12-15) BENZOATE; CALENDULA OFFICINALIS FLOWER; GREEN TEA LEAF; MEDIUM-CHAIN TRIGLYCERIDES; CARBOMER HOMOPOLYMER, UNSPECIFIED TYPE; CETOSTEARYL ALCOHOL; CETEARYL GLUCOSIDE; CHAMOMILE; CITRIC ACID MONOHYDRATE; WATERMELON; COCONUT; DECYL GLUCOSIDE; DODECANE; GLYCERIN; GLYCERYL MONOCAPRYLATE; GLYCERYL STEARATE SE; SUNFLOWER OIL; LAMINARIA DIGITATA; PALMITOYL TETRAPEPTIDE-7; PALMITOYL TRIPEPTIDE-1; AVOCADO; POLYSORBATE 20; POTASSIUM SORBATE; PROPANEDIOL; HYALURONATE SODIUM; SODIUM STEAROYL GLUTAMATE; STEARIC ACID; SUCROSE; STARCH, TAPIOCA; TOCOPHEROL; TRIDECYL SALICYLATE; WATER; XANTHAN GUM

Kiss My Face Purely Mineral Face Factor 50 Sunscreen SPF 50

Active Ingredient

Zinc Oxide 17.50%

Purpose

Sunscreen

Uses:

- Helps prevent sunburn.
- higher SPF gives more sunburn protection
- retains SPF after 80 minutes of swimming or sweating
- If used as directed with other sun protection measures (see Directions), decreases risk of skin cancer and early skin aging caused by the sun.

Warnings:

For external use only

Do not use

- on damaged or broken skin.

When using this product,

- keep out of eyes. Rinse with water to remove.

Stop use and ask a doctor if

- rash or irritation develops and lasts.

Keep out of reach of children.

- If swallowed, get medical help or contact a Poison Control Center right away.

If pregnant or breast-feeding,

ask a health professional before use

Directions.

- Apply liberally 15 minutes before sun exposure and as needed.
- Children under 6 months of age: ask a doctor.
- Reapply:
- after 80 minutes of swimming or sweating
- immediately after towel drying
- at least every 2 hours
- Sun Protection Measures:Spending time in the sun increases your risk of skin cancer and early skin aging. To decrease the risk, regularly use a sunscreen with broad spectrum SPF 15 or higher and other sun protection measures including:
- Limit time in sun, especially from 10a.m.- 2 p.m.
- Wear long-sleeved shirts, pants, hats and sunglasses.

Other Information

- Protect the product in this container from excessive heat and direct sun.

Inactive Ingredients

Acetic Acid, Acetyl Hexapeptide-8, Aloe Barbadensis Leaf Juice, Argania Spinosa Kernel Oil, Ascorbic Acid, Butylene Glycol, Butylene Glycol, Butyrospermum Parkii (Shea) Butter, C12-15 Alkyl Benzoate, Calendula Officinalis Extract, Camellia Sinensis Leaf Extract, Caprylic/Capric Triglyceride, Carbomer, Cetearyl Alcohol, Cetearyl Glucoside, Chamomilla Recutlta (Matricaria) Flower Extract, Citric Acid, Citrullus Lanatus (Watermelon) Fruit Extract, Cocos Nucifera (Coconut) Oil, Decyl Glucoside, Dodecane, Glycerin, Glyceryl Caprylate, Glyceryl Stearate SE, Glyceryl Undecylenate, Helianthus Annuus (Sunflower) Seed Oil, Laminaria Digitata Extract, Palmitoyl Tetrapeptide-7, Palmitoyl Tripeptide-1, Persea Gratissima (Avacado) Oil, Polyhydroxvstearic Acid, Polysorbate 20, Potassium Sorbate, Propanediol, Sodium Hyaluronate, Sodium Stearoyl Glutamate, Stearic Acid, Sucrose, Tapioca Starch, Tocopherol, Tridecyl Salicylate, Water (Aqua), Xanthan Gum, Xanthophylls

Questions?

(800) 822-4320